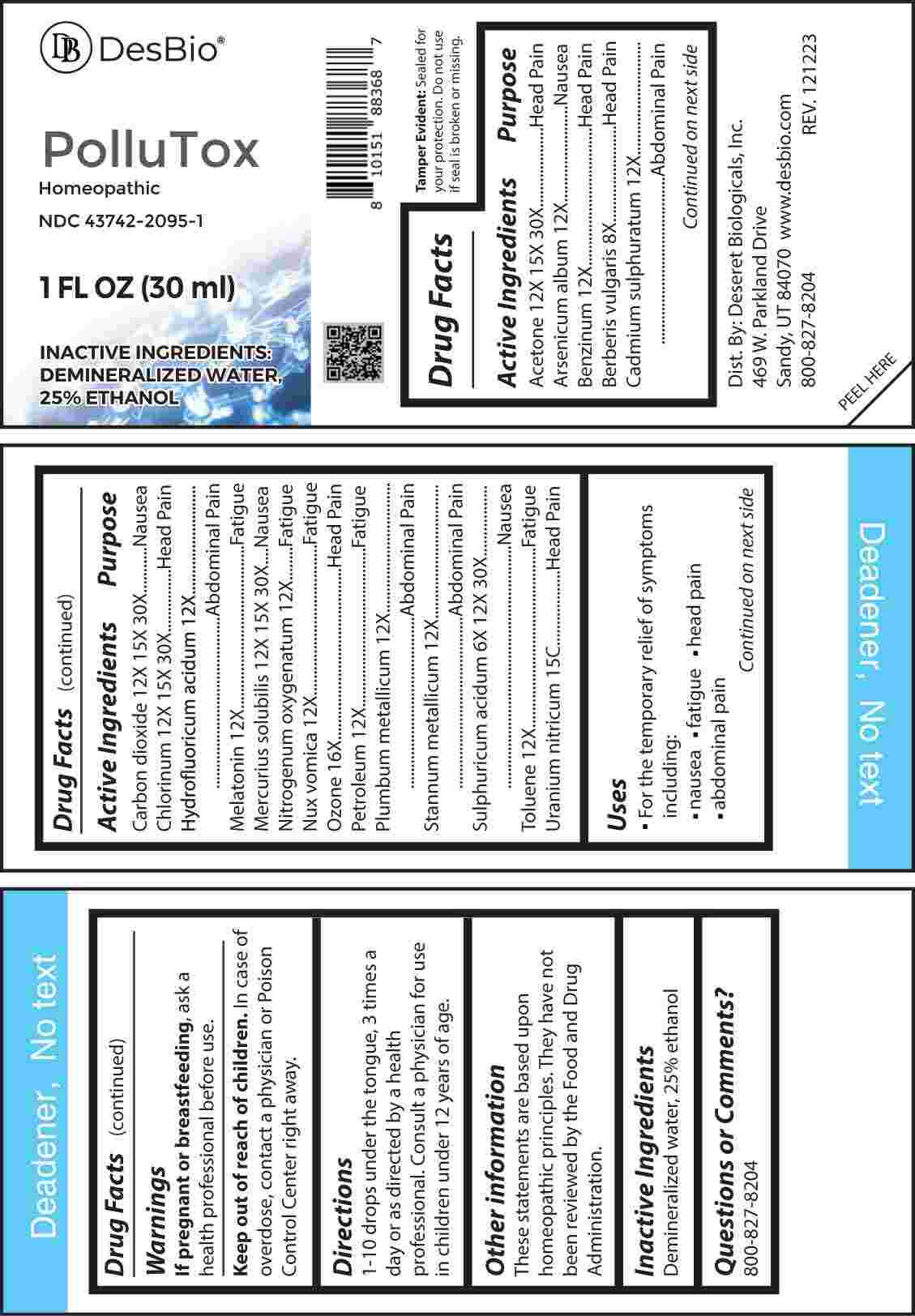 DRUG LABEL: Pollutox
NDC: 43742-2095 | Form: LIQUID
Manufacturer: Deseret Biologicals, Inc.
Category: homeopathic | Type: HUMAN OTC DRUG LABEL
Date: 20240327

ACTIVE INGREDIENTS: SULFURIC ACID 6 [hp_X]/1 mL; BERBERIS VULGARIS ROOT BARK 8 [hp_X]/1 mL; ARSENIC TRIOXIDE 12 [hp_X]/1 mL; BENZENE 12 [hp_X]/1 mL; CADMIUM SULFIDE 12 [hp_X]/1 mL; HYDROFLUORIC ACID 12 [hp_X]/1 mL; MELATONIN 12 [hp_X]/1 mL; NITROUS OXIDE 12 [hp_X]/1 mL; STRYCHNOS NUX-VOMICA SEED 12 [hp_X]/1 mL; KEROSENE 12 [hp_X]/1 mL; LEAD 12 [hp_X]/1 mL; TIN 12 [hp_X]/1 mL; TOLUENE 12 [hp_X]/1 mL; ACETONE 12 [hp_X]/1 mL; CARBON DIOXIDE 12 [hp_X]/1 mL; CHLORINE 12 [hp_X]/1 mL; MERCURIUS SOLUBILIS 12 [hp_X]/1 mL; OZONE 16 [hp_X]/1 mL; URANYL NITRATE HEXAHYDRATE 15 [hp_C]/1 mL
INACTIVE INGREDIENTS: WATER; ALCOHOL

DRUG FACTS:

ACTIVE INGREDIENTS:

Acetone 12X, 15X, 30X, Arsenicum Album 12X, Benzinum 12X, Berberis Vulgaris 8X, Cadmium Sulphuratum 12X, Carbon Dioxide 12X, 15X, 30X, Chlorinum 12X, 15X, 30X, Hydrofluoricum Acidum 12X, Melatonin 12X, Mercurius Solubilis 12X, 15X, 30X, Nitrogenum Oxygenatum 12X, Nux Vomica 12X, Ozone 16X, Petroleum 12X, Plumbum Metallicum 12X, Stannum Metallicum 12X, Sulphuricum Acidum 6X, 12X, 30X, Toluene 12X, Uranium Nitricum 15C.

PURPOSE:

Acetone-Head Pain, Arsenicum Album - Nausea, Benzinum – Head Pain, Berberis Vulgaris – Head Pain, Cadmium Sulphuratum – Abdominal Pain, Carbon Dioxide - Nausea, Chlorinum – Head Pain, Hydrofluoricum Acidum – Abdominal Pain, Melatonin - Fatigue, Mercurius Solubilis - Nausea, Nitrogenum Oxygenatum - Fatigue, Nux Vomica - Fatigue, Ozone – Head Pain, Petroleum - Fatigue, Plumbum Metallicum – Abdominal Pain, Stannum Metallicum – Abdominal Pain, Sulphuricum Acidum - Nausea, Toluene - Fatigue, Uranium Nitricum – Head Pain

USES:

• For the temporary relief of symptoms including:

• nausea • fatigue • head pain • abdominal pain

These statements are based upon homeopathic principles. They have not been reviewed by the Food and Drug Administration.

WARNINGS:

If pregnant or breast-feeding, ask a health professional before use.

Keep out of reach of children. In case of overdose, contact a physician or Poison Control Center right away.

Tamper Evident: Sealed for your protection. Do not use if seal is broken or missing.

KEEP OUT OF REACH OF CHILDREN:

In case of overdose, contact a physician or Poison Control Center right away.

DIRECTIONS:

1-10 drops under the tongue, 3 times a day or as directed by a health professional. Consult a physician for use in children under 12 years of age.

INACTIVE INGREDIENTS:

Demineralized water, 25% ethanol

QUESTIONS:

Dist. By: Deseret Biologicals, Inc.

469 W. Parkland Drive

Sandy, UT 84070

www.desbio.com

800-827-8204

PACKAGE LABEL DISPLAY:

Des Bio

PolluTox

Homeopathic
NDC 43742-2095-1
1 FL OZ (30 ml)